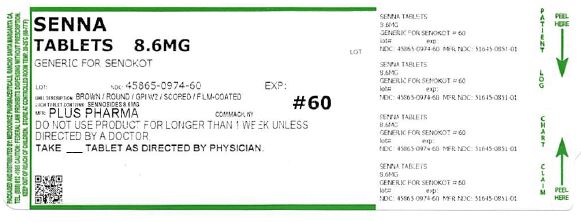 DRUG LABEL: Senna
NDC: 45865-974 | Form: TABLET, FILM COATED
Manufacturer: medsource pharmaceuticals
Category: otc | Type: HUMAN OTC DRUG LABEL
Date: 20191230

ACTIVE INGREDIENTS: SENNOSIDES 8.6 mg/1 1
INACTIVE INGREDIENTS: CALCIUM CARBONATE; CROSCARMELLOSE SODIUM; SODIUM SULFATE; HYPROMELLOSE, UNSPECIFIED; MAGNESIUM STEARATE; MALTODEXTRIN; CELLULOSE, MICROCRYSTALLINE; PROPYLENE GLYCOL; SILICON DIOXIDE; STEARIC ACID; TRIACETIN

Senna Tablets

Active ingredient (in each tablet)

Sennosides 8.6 mg

Purpose

Laxative

Uses

- relieves occasional constipation (irregularity)
- generally produces a bowel movement in 6-12 hours

Warnings

Do not use

- laxative products for longer than 1 week unless directed by a doctor

Ask a doctor before use if you have

- stomach pain
- nausea
- vomiting
- noticed a sudden change in bowel habits that continues over a period of 2 weeks

Stop use and ask a doctor if

you have rectal bleeding or fail to have a bowel movement after use of a laxative.

These may indicate a serious condition.

If pregnant or breast-feeding,

ask a health professional before use.

Keep out of reach of children.

In case of overdose, get medical help or contact a Poison Control Center right away.

Directions

- take preferably at bedtime or as directed by a doctor

age | starting dosage | maximum dosage
adults and children 12 years of age and older | 2 tablets once a day | 4 tablets twice a day
children 6 to under 12 years of age | 1 tablet once a day | 2 tablets twice a day
children 2 to under 6 years of age | 1/2 tablet once a day | 1 tablet twice a day
children under 2 years | ask a doctor | ask a doctor

Other information

- Each tablet contains: Calcium 20 mg
- Store at room temperature
- Do not use if imprinted seal under cap is broken or missing

Inactive ingredients

Calcium carbonate, croscarmellose sodium, hypromellose, magnesium stearate, maltodextrin, microcrystalline cellulose, propylene glycol, silicon dioxide, sodium sulfate, stearic acid, triacetin.

Questions?

If you have any questions or comments,or to report an adverse event, please contact (800) 795-9775.